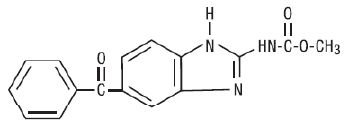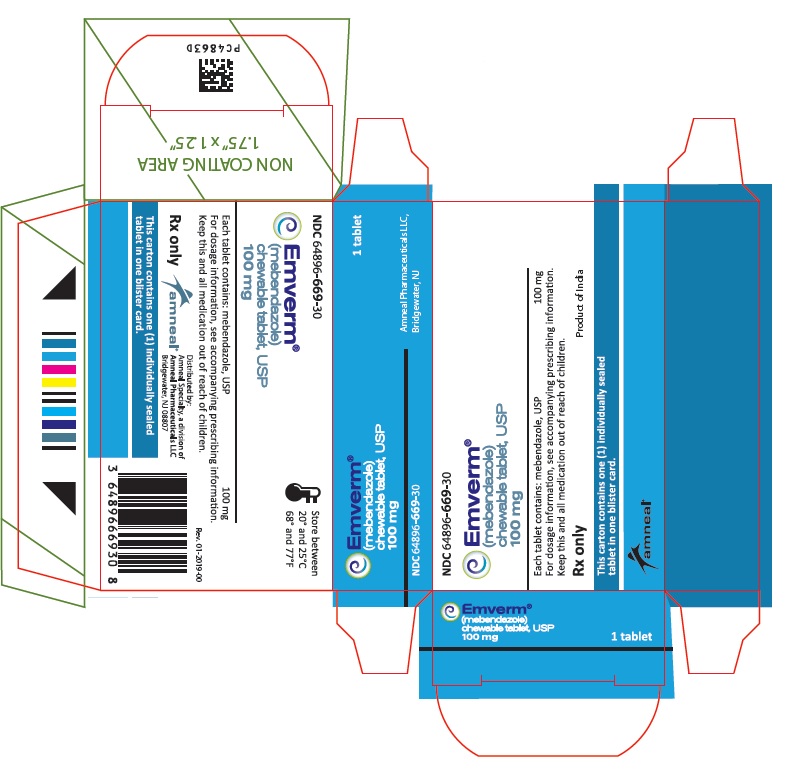 DRUG LABEL: Emverm
NDC: 64896-669 | Form: TABLET, CHEWABLE
Manufacturer: Amneal Pharmaceuticals LLC
Category: prescription | Type: HUMAN PRESCRIPTION DRUG LABEL
Date: 20210823

ACTIVE INGREDIENTS: MEBENDAZOLE 100 mg/1 1
INACTIVE INGREDIENTS: MAGNESIUM STEARATE; MICROCRYSTALLINE CELLULOSE; ANHYDROUS LACTOSE; STEARIC ACID; SODIUM LAURYL SULFATE; SACCHARIN SODIUM; FD&C YELLOW NO. 6; STARCH, CORN; SODIUM STARCH GLYCOLATE TYPE A POTATO

HIGHLIGHTS OF PRESCRIBING INFORMATION

These highlights do not include all the information needed to use EMVERM® safely and effectively. See full prescribing information for EMVERM®.
EMVERM® (mebendazole) chewable tablets, for oral use
Initial U.S. Approval: 1974

1 INDICATIONS AND USAGE

EMVERM® is an anthelmintic indicated for the treatment of patients two years of age and older with gastrointestinal infections caused by:

- Ancylostoma duodenale (hookworm),
- Ascaris lumbricoides (roundworm),
- Enterobius vermicularis (pinworm),
- Necator americanus (hookworm), and
- Trichuris trichiura (whipworm), (1).

2 DOSAGE AND ADMINISTRATION

Adults and Pediatrics: The tablet may be chewed, swallowed, or crushed and mixed with food (2).

 | Pinworm (enterobiasis) | Whipworm (trichuriasis) | Roundworm (ascariasis) | Hookworm
Dose | 1 tablet once | 1 tablet morning and evening for 3 consecutive days | 1 tablet morning and evening for 3 consecutive days | 1 tablet morning and evening for 3 consecutive days

3 DOSAGE FORMS AND STRENGTHS

- Chewable Tablet: 100 mg (3)

4 CONTRAINDICATIONS

- Patients with a known hypersensitivity to the drug or its excipients (4)

5 WARNINGS AND PRECAUTIONS

- Risk of Convulsions: Convulsions in infants below the age of 1 year have been reported (5.1).
- Hematologic Effects: Neutropenia and agranulocytosis have been reported in patients receiving mebendazole at higher doses and for prolonged duration. Monitor blood counts in these patients (5.2).
- Metronidazole and Serious Skin Reactions: Stevens-Johnson syndrome/toxic epidermal necrolysis (SJS/TEN) have been reported with the concomitant use of mebendazole and metronidazole. Avoid concomitant use of mebendazole and metronidazole (5.3).

6 ADVERSE REACTIONS

Adverse reactions reported in clinical trials were anorexia, abdominal pain, diarrhea, flatulence, nausea, vomiting and rash (6.1).

To report SUSPECTED ADVERSE REACTIONS, contact Amneal Pharmaceuticals at 1-877-835-5472 or FDA at 1-800-FDA-1088 or www.fda.gov/medwatch.

FULL PRESCRIBING INFORMATION

1 INDICATIONS AND USAGE

EMVERM® is indicated for the treatment of patients two years of age and older with gastrointestinal infections caused by Ancylostoma duodenale (hookworm), Ascaris lumbricoides (roundworm), Enterobius vermicularis (pinworm), Necator americanus (hookworm), and Trichuris trichiura (whipworm).

2 DOSAGE AND ADMINISTRATION

The recommended dosage for EMVERM® is described in Table 1 below. The same dosage schedule applies to adults and pediatric patients two years of age and older. The tablet may be chewed, swallowed, or crushed and mixed with food.

Table 1: Dosage of EMVERM in Adult and Pediatric Patients (two years of age and older)

 | Pinworm (enterobiasis) | Whipworm (trichuriasis) | Roundworm (ascariasis) | Hookworm
Dose | 1 tablet once | 1 tablet morning and evening for 3 consecutive days | 1 tablet morning and evening for 3 consecutive days | 1 tablet morning and evening for 3 consecutive days

If the patient is not cured three weeks after treatment, a second course of treatment is advised. No special procedures, such as fasting or purging, are required.

3 DOSAGE FORMS AND STRENGTHS

EMVERM® (mebendazole) Chewable Tablet, USP: 100 mg, round, light peach-colored, unscored, debossed “ap” above “107” on one side and plain on the other side.

4 CONTRAINDICATIONS

EMVERM® is contraindicated in persons with a known hypersensitivity to the drug or its excipients.

5 WARNINGS AND PRECAUTIONS

5.1 Risk of Convulsions

Although EMVERM® is approved for use in children two years of age and older, convulsions have been reported in infants below the age of 1 year during post-marketing experience with mebendazole, including EMVERM® [see Adverse Reactions (6.2) and Use in Specific Populations (8.4)].

5.2 Hematologic Effects

Agranulocytosis and neutropenia have been reported with mebendazole use at higher doses and for more prolonged durations than is recommended for the treatment of soil-transmitted helminth infections. Monitor blood counts if EMVERM® is used at higher doses or for prolonged duration.

5.3 Metronidazole Drug Interaction and Serious Skin Reactions

Stevens-Johnson syndrome/toxic epidermal necrolysis (SJS/TEN) have been reported with the concomitant use of mebendazole and metronidazole. Avoid concomitant use of mebendazole, including EMVERM® and metronidazole.

6 ADVERSE REACTIONS

6.1 Clinical Studies

Because clinical trials are conducted under widely varying conditions, adverse reaction rates observed in the clinical trials of a drug cannot be directly compared to rates in the clinical trials of another drug and may not reflect the rates observed in practice.

The safety of mebendazole was evaluated in 6276 subjects who participated in 39 clinical trials for treatment of single or mixed parasitic infections of the gastrointestinal tract. In these trials, the formulations, dosages and duration of mebendazole treatment varied. Adverse reactions reported in mebendazole-treated subjects from the 39 clinical trials are shown in Table 2 below.

Table 2: Adverse Reactions Reported in Mebendazole-treated Subjects from 39 Clinical Trials*

Adverse Reaction(s)

Gastrointestinal Disorders

Anorexia

Abdominal Pain

Diarrhea

Flatulence

Nausea

Vomiting

Skin and Subcutaneous Tissue Disorders

Rash

*Includes mebendazole formulations, dosages and treatment duration other than EMVERM® 100 mg tablet

6.2 Postmarketing Experience

The following adverse reactions have been identified in adult and pediatric patients postmarketing with mebendazole formulations and dosages other than the EMVERM® 100 mg chewable tablet. Because these reactions are reported voluntarily from a population of uncertain size, it is not always possible to reliably estimate their frequency or establish a causal relationship to drug exposure.

Table 3: Adverse Reactions Identified During Postmarketing Experience with Mebendazole*

 | Adverse Reaction(s)
Blood and Lymphatic System Disorders | Agranulocytosis, Neutropenia
Immune System Disorders | Hypersensitivity including anaphylactic reactions
Nervous System Disorders | Convulsions, Dizziness
Hepatobiliary Disorders | Hepatitis, Abnormal liver tests
Renal and Urinary Disorders | Glomerulonephritis
Skin and Subcutaneous Tissue Disorders | Toxic epidermal necrolysis, Stevens-Johnson syndrome, Exanthema, Angioedema, Urticaria, Alopecia

*Includes mebendazole formulations, dosages and treatment duration other than EMVERM® 100 mg chewable tablets

7 DRUG INTERACTIONS

Concomitant use of mebendazole, including EMVERM®, and metronidazole should be avoided [see Warnings and Precautions (5.3)].

8 USE IN SPECIFIC POPULATIONS

8.1 Pregnancy

Risk Summary

The available published literature on mebendazole use in pregnant women has not reported a clear association between mebendazole and a potential risk of major birth defects or miscarriages [see Data]. There are risks to the mother and fetus associated with untreated helminthic infection during pregnancy [see Clinical Considerations].

In animal reproduction studies, adverse developmental effects (i.e., skeletal malformations, soft tissue malformations, decreased pup weight, embryolethality) were observed when mebendazole was administered to pregnant rats during the period of organogenesis at single oral doses as low as 10 mg/kg (approximately 0.5-fold the total daily maximum recommended human dose [MRHD]). Maternal toxicity was present at the highest of these doses [see Data].

The estimated background risk of major birth defects and miscarriage for the indicated populations is unknown. All pregnancies have a background risk of birth defect, loss, or other adverse outcomes. In the U.S. general population, the estimated background risk of major birth defects and miscarriage in clinically recognized pregnancies is 2-4% and 15-20%, respectively.

Clinical Considerations

Disease-Associated Maternal and/or Embryo/Fetal Risks

Untreated soil transmitted helminth infections in pregnancy are associated with adverse outcomes including maternal iron deficiency anemia, low birth weight, neonatal and maternal death.

Data

Human Data

Several published studies, including prospective pregnancy registries, case-control, retrospective cohort, and randomized controlled studies, have reported no association between mebendazole use and a potential risk of major birth defects or miscarriage. Overall, these studies did not identify a specific pattern or frequency of major birth defects with mebendazole use. However, these studies cannot definitely establish the absence of any mebendazole-associated risk because of methodological limitations, including recall bias, confounding factors and, in some cases, small sample size or exclusion of first trimester mebendazole exposures.

Animal Data

Embryo-fetal developmental toxicity studies in rats revealed no adverse effects on dams or their progeny at doses up to 2.5 mg/kg/day on gestation days 6–15 (the period of organogenesis). Dosing at ≥10 mg/kg/day resulted in a lowered body weight gain and a decreased pregnancy rate. Maternal toxicity, including body weight loss in one animal and maternal death in 11 of 20 animals, was seen at 40 mg/kg/day. At 10 mg/kg/day, increased embryo-fetal resorption (100% were resorbed at 40 mg/kg/day), decreased pup weight and increased incidence of malformations (primarily skeletal) were observed. Mebendazole was also embryotoxic and teratogenic in pregnant rats at single oral doses during organogenesis as low as 10 mg/kg (approximately 0.5-fold the total daily MRHD, based on mg/m^2).

In embryo-fetal developmental toxicity studies in mice dosed on gestation days 6–15, doses of 10 mg/kg/day and higher resulted in decreased body weight gain at 10 and 40 mg/kg/day and a higher mortality rate at 40 mg/kg/day. At doses of 10 mg/kg/day (approximately 0.2-fold the total daily MRHD, based on mg/m^2) and higher, embryo-fetal resorption increased (100% at 40 mg/kg) and fetal malformations, including skeletal, cranial, and soft tissue anomalies, were present. Dosing of hamsters and rabbits did not result in embryotoxicity or teratogenicity at doses up to 40 mg/kg/day (1.6 to 3.9-fold the total daily MRHD, based on mg/m^2).

In a peri- and post-natal toxicity study in rats, mebendazole did not adversely affect dams or their progeny at 20 mg/kg/day. At 40 mg/kg (1.9-fold the total daily MRHD, based on mg/m^2), a reduction of the number of live pups was observed and there was no survival at weaning. No abnormalities were found on gross and radiographic examination of pups at birth.

8.2 Lactation

Risk Summary

Limited data from case reports demonstrate that a small amount of mebendazole is present in human milk following oral administration. There are no reports of effects on the breastfed infant, and the limited reports on the effects on milk production are inconsistent. The limited clinical data during lactation precludes a clear determination of the risk of EMVERM® to a breastfed infant; therefore, developmental and health benefits of breastfeeding should be considered along with the mother's clinical need for EMVERM® and any potential adverse effects on the breastfed infant from EMVERM® or from the underlying maternal condition.

8.4 Pediatric Use

The safety and effectiveness of EMVERM® 100 mg chewable tablets has not been established in pediatric patients less than two years of age. Convulsions have been reported with mebendazole use in children less than one year of age [see Warnings and Precautions (5.1) and Adverse Reactions (6.2)].

8.5 Geriatric Use

Clinical studies of mebendazole did not include sufficient numbers of subjects aged 65 and older to determine whether they respond differently from younger subjects.

10 OVERDOSAGE

In patients treated at dosages substantially higher than recommended or for prolonged periods of time, the following adverse reactions have been reported: alopecia, reversible transaminase elevations, hepatitis, agranulocytosis, neutropenia, and glomerulonephritis.

Symptoms and signs

In the event of accidental overdose, gastrointestinal signs/symptoms may occur.

Treatment

There is no specific antidote.

11 DESCRIPTION

EMVERM® (mebendazole) is an orally administered, synthetic anthelmintic available as chewable tablets, each containing 100 mg of mebendazole, USP. Inactive ingredients are: microcrystalline cellulose, corn starch, anhydrous lactose NF, sodium starch glycolate, magnesium stearate, stearic acid, sodium lauryl sulfate, sodium saccharin, and FD&C Yellow #6.

Chemically, mebendazole is methyl 5-benzoylbenzimidazole-2-carbamate with a molecular formula of C16H13N3O3 and the following structural formula:

Mebendazole, USP is a white to slightly yellow powder with a molecular weight of 295.29. It is less than 0.05% soluble in water, dilute mineral acid solutions, alcohol, ether and chloroform, but is soluble in formic acid.

12 CLINICAL PHARMACOLOGY

12.1 Mechanism of Action

Mebendazole, a benzimidazole, is an anthelmintic drug [see Microbiology (12.4)].

12.3 Pharmacokinetics

Absorption

Following oral administration of mebendazole, the majority of the dose remains in the gastrointestinal tract where it exerts an anthelmintic effect locally. Following administration of 100 mg twice daily for three consecutive days, plasma concentrations of EMVERM® (mebendazole) and its primary metabolite, the 2-amine hydrolyzed metabolite, do not exceed 0.03 mcg/mL and 0.09 mcg/mL, respectively. Dosing with a high fat meal increases the bioavailability of mebendazole, although the overall effect of food on the amount of drug remaining in the gastrointestinal tract is not expected to be substantial.

Distribution

The plasma protein binding of mebendazole is 90 to 95%. The volume of distribution is 1 to 2 L/kg, indicating that absorbed mebendazole penetrates areas outside the vascular space.

Metabolism

Orally administered mebendazole is extensively metabolized primarily by the liver. Plasma concentrations of its major metabolites (hydrolyzed and reduced forms of mebendazole) are higher than those of mebendazole. All metabolites are devoid of anthelmintic activity. Impaired hepatic function, impaired metabolism, or impaired biliary elimination may lead to higher plasma concentrations of mebendazole.

Excretion

Mebendazole, the conjugated forms of mebendazole, and its metabolites likely undergo some degree of enterohepatic recirculation. The apparent elimination half-life after an oral dose ranges from 3 to 6 hours in most patients. Less than 2% of orally administered mebendazole is excreted in urine and the remainder in the feces as unchanged drug or its metabolites.

12.4 Microbiology

Mechanism of Action

Mebendazole interferes with cellular tubulin formation in the helminth and causes ultrastructural degenerative changes in its intestine. As a result, its glucose uptake and the digestive and reproductive functions are disrupted, leading to immobilization, inhibition of egg production and death of the helminth.

Antimicrobial Activity

Mebendazole is active against:

Ancylostoma duodenale

Ascaris lumbricoides

Enterobius vermicularis

Necator americanus

Trichuris trichiura

Resistance

There is a potential for development of resistance to mebendazole. The mechanism of resistance to mebendazole is likely due to changes of beta-tubulin protein, which reduces binding of mebendazole to beta-tubulin; however, the clinical significance of this is not known.

13 NONCLINICAL TOXICOLOGY

13.1 Carcinogenesis, Mutagenesis, Impairment of Fertility

In carcinogenicity tests of mebendazole in mice and rats, no carcinogenic effects were seen at doses as high as 40 mg/kg (one to two times the human dose, based on mg/m^2) given daily over two years. No mutagenic activity was observed with mebendazole in a bacterial reverse gene mutation test. Mebendazole was mutagenic in the absence of S-9 when tested using a continuous (24 hour) treatment incubation period in the mouse lymphoma thymidine kinase assay. Mebendazole was aneugenic in vitro in mammalian somatic cells. In the in vivo mouse micronucleus assay, orally administered mebendazole induced an increased frequency of micronucleated polychromatic erythrocytes with evidence suggestive of aneugenicity. Doses up to 40 mg/kg in rats (2 times the total daily human dose, based on mg/m^2), given to males for 60 days and to females for 14 days prior to gestation, had no effect upon fetuses and offspring.

14 CLINICAL STUDIES

Efficacy rates derived from various studies are shown in Table 4 below:

Table 4: Mean Cure Rates and Egg Reductions from Clinical Studies

 | Pinworm (enterobiasis) | Whipworm (trichuriasis) | Roundworm (ascariasis) | Hookworm
Cure rates mean | 95% | 68% | 98% | 96%
Egg reduction mean | - | 93% | 99% | 99%

16 HOW SUPPLIED/STORAGE AND HANDLING

EMVERM® (mebendazole) Chewable Tablet, USP is available as a 100 mg, round, light peach-colored, unscored, debossed “ap” above “107” on one side and plain on the other side. They are supplied as follows:

Blister package of 1 tablet NDC 64896-669-30

Store at 68° to 77°F (20° to 25°C) [See USP Controlled Room Temperature].

17 PATIENT COUNSELING INFORMATION

Advise the patient to read the FDA-approved patient labeling (Patient Information).

Advise patients that:

- Taking EMVERM® and metronidazole together may cause serious skin reactions and should be avoided [see Warning and Precautions (5.3)].
- EMVERM® can be taken with or without food [see Dosage and Administration (2)].

Manufactured by:
Alcami
Wilmington, NC 28405

Distributed by:
Amneal Specialty, a division of
Amneal Pharmaceuticals LLC
Bridgewater, NJ 08807
Rev. 08-2021-01

PATIENT INFORMATION

EMVERM® (EM-verm)

(mebendazole) Chewable Tablets USP, for oral use

What is EMVERM?
Emverm is a prescription medicine used to treat adults and children 2 years of age and older with intestinal worm infections caused by pinworm, whipworm, roundworm, or hookworm.

Who should not take EMVERM?
Do not take Emverm if you are allergic to mebendazole or any of the ingredients in Emverm. See the end of this leaflet for a complete list of ingredients in Emverm.

Before you take EMVERM, tell your healthcare provider about all of your medical conditions, including if you:

- are pregnant or plan to become pregnant. It is not known if EMVERM will harm your unborn baby.
- are breastfeeding or plan to breastfeed. EMVERM can pass into your milk and may harm your baby. Talk to your healthcare provider about the best way to feed your baby if you take EMVERM. Do not breastfeed while taking EMVERM.

Tell your healthcare provider about all the medicines you take, including prescription and over-the-counter medicines, vitamins, and herbal supplements.
Using EMVERM with certain other medicines can change the way these medicines act, causing serious side effects.
Know the medicines you take. Keep a list of them to show to your healthcare provider or pharmacist when you get a new medicine.

How should I take EMVERM?

- Take EMVERM exactly as your healthcare provider tells you to take it.
- Take EMVERM by mouth with or without food.
- EMVERM tablets may be chewed, swallowed, or crushed and mixed with food.
- If you take too much EMVERM, you might have symptoms that include stomach cramps, nausea, vomiting or diarrhea.

What should I avoid while taking EMVERM?
Do not take Emverm with metronidazole (a medicine used to treat bacterial and protozoan infections) as serious skin reactions called Stevens-Johnson syndrome (SJS) and toxic epidermal necrolysis (TEN) can happen.

What are the possible side effects of EMVERM?
EMVERM may cause serious side effects, including:

- Low white blood cell count (neutropenia). Neutropenia can cause you to get other infections. Your healthcare provider will check your blood count regularly during your treatment with EMVERM. Tell your healthcare provider right away if you have a fever or any signs of an infection while taking EMVERM
- Severe skin reactions (Stevens-Johnson syndrome and toxic epidermal necrolysis). EMVERM may cause rare, but serious skin reactions when taken with metronidazole and other medicines that contain mebendazole. These severe allergic reactions may be life-threatening and need to be treated in a hospital. Call your healthcare provider right away or get emergency medical help if you have any allergic reactions or the following symptoms:
  - severe skin blisters
  - sores around the mouth, nose, eyes, vagina or penis (genitals)
  - peeling skin
  - swollen face, lips, mouth, tongue or throat
  - itchy rash (hives)

The most common side effects of EMVERM include:

- loss of appetite (anorexia)
- stomach pain
- diarrhea
- passing gas
- nausea
- vomiting
- rash

Tell your healthcare provider if you have any side effect that bothers you or does not go away.
These are not all the possible side effects of EMVERM.
Call your doctor for medical advice about side effects. You may report side effects to FDA at 1-800-FDA-1088.

How should I store EMVERM?

- Store at room temperature between 68°F to 77°F (20°C to 25°C).
- Safely throw away medicine that is out of date or no longer needed.

Keep EMVERM and all medicines out of the reach of children.

General information about the safe and effective use of EMVERM.
Medicines are sometimes prescribed for purposes other than those listed in a Patient Information leaflet. Do not use EMVERM for a condition for which it was not prescribed. Do not give EMVERM to other people, even if they have the same symptoms that you have. It may harm them. You can ask your pharmacist or healthcare provider for information about EMVERM that is written for health professionals.

What are the ingredients in EMVERM?

Active ingredient: mebendazole, USP.
Inactive ingredients: microcrystalline cellulose, corn starch, anhydrous lactose NF, sodium starch glycolate, magnesium stearate, stearic acid, sodium lauryl sulfate, sodium saccharin, and FD&C Yellow #6.
Manufactured by:
Alcami
Wilmington, NC 28405
Distributed by:
Amneal Specialty, a division of
Amneal Pharmaceuticals LLC
Bridgewater, NJ 08807
For more information, call Amneal Pharmaceuticals at 1-877-835-5472.

This Patient Information has been approved by the U.S. Food and Drug Administration.

Rev. 08-2021-01